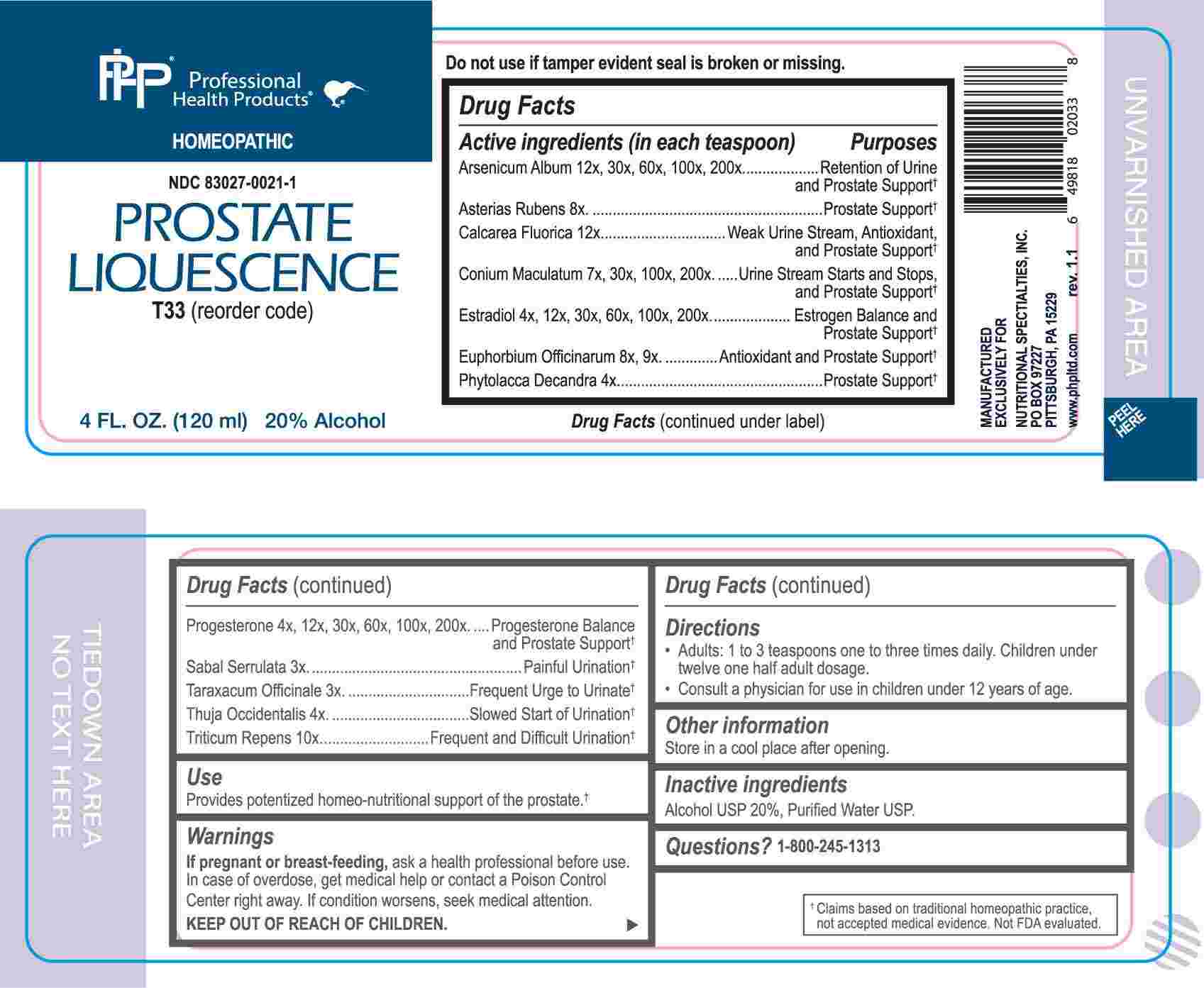 DRUG LABEL: Prostate Liquescence
NDC: 83027-0021 | Form: LIQUID
Manufacturer: Nutritional Specialties, Inc.
Category: homeopathic | Type: HUMAN OTC DRUG LABEL
Date: 20250407

ACTIVE INGREDIENTS: SAW PALMETTO 3 [hp_X]/1 mL; TARAXACUM OFFICINALE 3 [hp_X]/1 mL; PHYTOLACCA AMERICANA ROOT 4 [hp_X]/1 mL; THUJA OCCIDENTALIS LEAFY TWIG 4 [hp_X]/1 mL; ESTRADIOL 4 [hp_X]/1 mL; PROGESTERONE 4 [hp_X]/1 mL; CONIUM MACULATUM FLOWERING TOP 7 [hp_X]/1 mL; ASTERIAS RUBENS 8 [hp_X]/1 mL; EUPHORBIA RESINIFERA RESIN 8 [hp_X]/1 mL; ELYMUS REPENS ROOT 10 [hp_X]/1 mL; CALCIUM FLUORIDE 12 [hp_X]/1 mL; ARSENIC TRIOXIDE 12 [hp_X]/1 mL
INACTIVE INGREDIENTS: WATER; ALCOHOL

DRUG FACTS:

ACTIVE INGREDIENTS:

Arsenicum Album 12X, 30X, 60X, 100X, 200X, Asterias Rubens 8X, Calcarea Fluorica 12X, Conium Maculatum 7X, 30X, 100X, 200X, Estradiol 4X, 12X, 30X, 60X, 100X, 200X, Euphorbium Officinarum 8X, 9X, Phytolacca Decandra 4X, Progesterone 4X, 12X, 30X, 60X, 100X, 200, Sabal Serrulata 3X, Taraxacum Officinale 3X, Thuja Occidentalis 4X, Triticum Repens 10X.

PURPOSE:

Arsenicum Album – Retention of Urine and Prostate Support,† Asterias Rubens – Prostate Support,† Calcarea Fluorica – Weak Urine Stream, Antioxidant, and Prostate Support,† Conium Maculatum – Urine Stream Starts and Stops, and Prostate Support,† Estradiol – Estrogen Balance and Prostate Support,† Euphorbium Officinarum – Antioxidant and Prostate Support,† Phytolacca Decandra – Prostate Support,† Progesterone – Progesterone Balance and Prostate Support,† Sabal Serrulata – Painful Urination,† Taraxacum Officinale – Frequent Urge to Urinate,† Thuja Occidentalis – Slowed Start of Urination,† Triticum Repens – Frequent and Difficult Urination†

†Claims based on traditional homeopathic practice, not accepted medical evidence. Not FDA evaluated.

USES:

Provides potentized homeo-nutritional support of the prostate.†

†Claims based on traditional homeopathic practice, not accepted medical evidence. Not FDA evaluated.

WARNINGS:

If pregnant or breast-feeding, ask a health professional before use.

In case of overdose, get medical help or contact a Poison Control Center right away.

If condition worsens, seek medical attention.

KEEP OUT OF REACH OF CHILDREN

Do not use if tamper evident seal is broken or missing.

Store in a cool place after opening

KEEP OUT OF REACH OF CHILDREN:

In case of overdose, get medical help or contact a Poison Control Center right away.

DIRECTIONS:

• Adults: 1 to 3 teaspoons one to three times daily. Children under twelve one half adult dosage.

Consult a physician for use in children under 12 years of age.

INACTIVE INGREDIENTS:

Alcohol USP 20%, Purified Water USP.

QUESTIONS:

MANUFACTURED EXCLUSIVELY FOR

NUTRITIONAL SPECIALTIES, INC.

PO BOX 97227

PITTSBURG, PA 15229

www.phpltd.com

1-800-245-1313

PACKAGE LABEL DISPLAY:

Professional

Health Products

HOMEOPATHIC

NDC 83027-0021-1

PROSTATE

LIQUESCENCE

4 FL. OZ (120 ml)